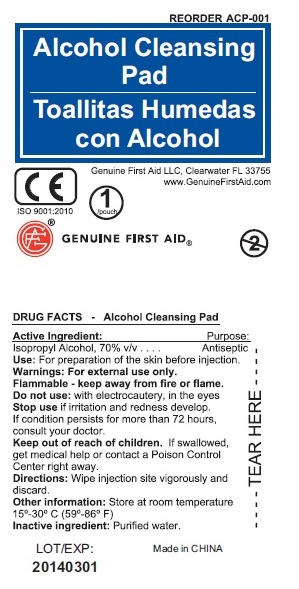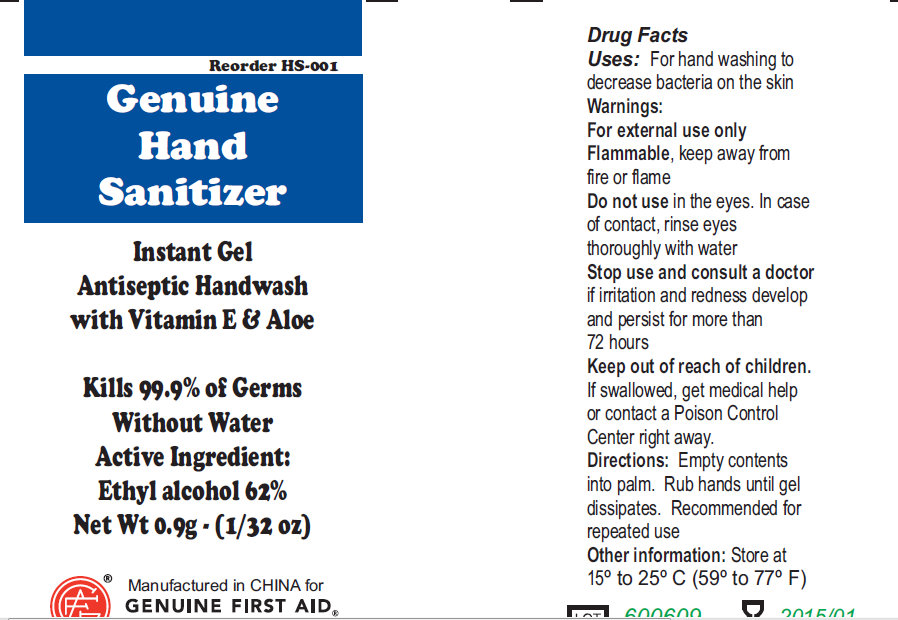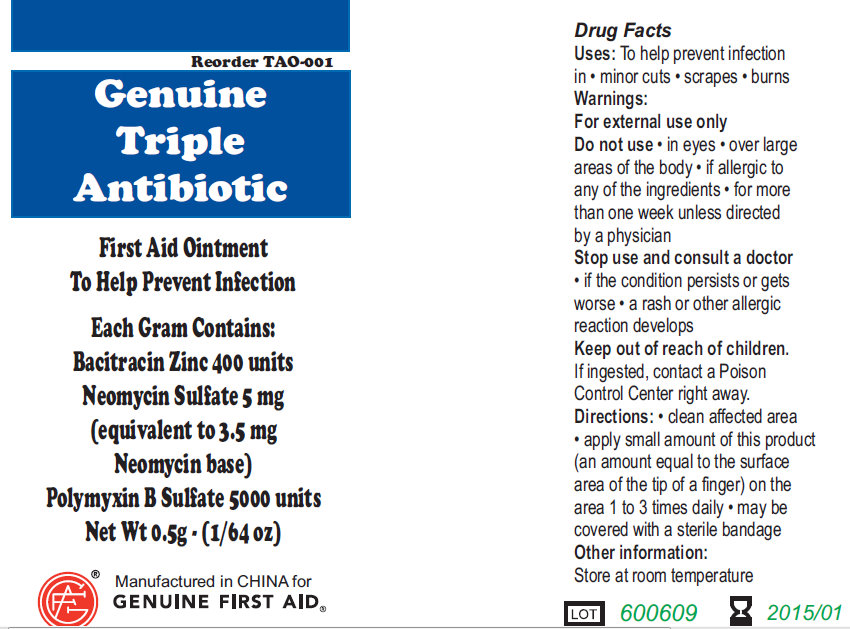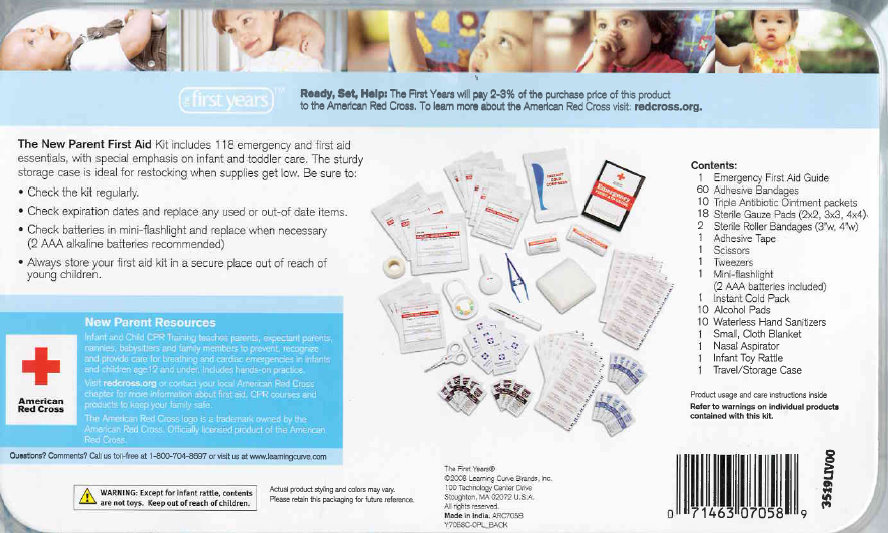 DRUG LABEL: The New Parent  First Aid
NDC: 52164-1120 | Form: KIT | Route: TOPICAL
Manufacturer: American Red Cross
Category: otc | Type: HUMAN OTC DRUG LABEL
Date: 20100607

ACTIVE INGREDIENTS: BACITRACIN ZINC 400 [iU]/1 g; NEOMYCIN SULFATE 5 mg/1 g; POLYMYXIN B SULFATE 5000 [iU]/1 g; ISOPROPYL ALCOHOL 70 mL/100 mL; ALCOHOL 62 g/100 g
INACTIVE INGREDIENTS: WATER

The New Parent First Aid

Active Ingredient: .........Bacitracin Zinc 400 units
Neomycin Sulfate 5mg (equivalent to 3.5 mg Neomycin base)
Polymyxin B Sulfate 5000 units

PURPOSE

Uses: To help prevent infection in:
minor cuts; scrapes; burns

Warnings:
For external use only.

Do not use: in eyes; over large areas of the body;
If allergic to any of the ingredients; for more than one week unless directed by a physician.

Stop use and consult a doctor:
if the condition persists or gets worse; a rash or other allergic reaction develops

Keep out of reach of children.
If ingested, contact a Poison
Control Center right away.

WHEN USING

Directions: clean affected area; apply small amount of this product (an amount equal to the surface area of the tip of a finger) on the area 1 to 3 times daily; may be covered with a sterile bandage

Other information:
Store at room temperature.

PACKAGE LABEL

Genuine Triple Antibiotic
First Aid Ointment
To Help Prevent Infection
Each Gram Contains:
Bacitracin Zinc 400 units
Neomycin Sulfate 5 mg
(equivalent to 3.5 mg
Neomycin base)
Polymyxin B Sulfate 5000 units
Net Wt. 0.5g ; (1/64 oz)
Manufactured in CHINA for
GENUINE FIRST AID.

Active Ingredient: Purpose
Isopropyl Alcohol, 70% v/v............... Antiseptic

PURPOSE

Use: For preparation of skin before injection.

Warnings: For external use only.

STORAGE AND HANDLING

Flammable - keep away from fire or flame
Store at room temperature 15-30 degree Celsius (59-86 degree Fahrenheit)

Do not use: with electrocautery, in the eyes.

Stop use if irritation and redness develop. If condition persists for more than 72 hours, consult your doctor.

Keep out of reach of children. If swallowed,
get medical help or contact a Poison Control
Center right away.

WHEN USING

Wipe Injection site vigorously and discard.

Inactive Ingredient: Purified water.

DESCRIPTION

LOT/EXP: Made in CHINA
20140301

PACKAGE LABEL

Alcohol Cleansing Pad
Genuine First Aid LLC, Clearwater FL 33755
www.GenuineFirstAid.com
1/pouch
GENUINE FIRST AID

Active Ingredient:
Ethyl Alcohol 62 percent

PURPOSE

Uses: For hand washing to decrease bacteria on the skin

Warnings:
For external use only
Flammable, keep away from fire or flame

Do not use in the eyes. In case of contact, rinse eyes thoroughly with water.

Stop use and consult a doctor if irritation and redness develop
and persist for more than 72 hours.

Keep out of reach of children.
If swallowed, get medical help or contact a Poison Control Center right away.

Directions:
Empty contents into palm. Rub hands until gel dissipates. Recommended for repeated use.

Other Information: Store at 15 to 25 degree Celsius (59 to 77 degree Fahrenheit)

PACKAGE LABEL

Genuine Hand Sanitizer
Instant Gel
Antiseptic Handwash
with Vitamin E and Aloe
Kills 99.9 percent of germs
Without Water
Active Ingredient:
Ethyl Alcohol 62 percent
Net Wt 0.9g (1/32 oz)
Manufactured in China For
Genuine First Aid.

PACKAGE LABEL

first years

Ready, Set, Help: The First Years will pay 2-3% of the purchase price of this product to the American Red Cross. To learn more about the American Red Cross visit: redcross.org

The New Parent First Aid Kit includes 118 emergency and first aid essentials, with special emphasis on infant and toddler care. The sturdy storage case is ideal for restocking when supplies get low. Be sure to:

-Check the kit regularly

-Check expiration dates and replace any used or out-of date items.

-Check batteries in mini-flash light and replace when necessary (2 AAA alkaline batteries recommended)

-Always store y our first aid kit in a secure place out of reach of young children

New Parent Resources
Infant and Child CPR Training teaches parents, expectant parents, nannies, babysitters and family members to prevent, recognize and provide care for breathing and cardiac emergencies in infants and children age 12 and under. Includes hands-on practice.

Visit redcross.org or contact your local American Red Cross chapter for more information about first aid, CPR courses and products to keep your family safe.

The American Red Cross logo is a trademark owned by the American Red Cross. Officially licensed product of the American Red Cross

Questions? Comments? Call us toll-free at 1-800-704-8697 or visit us at www.learningcurve.com

WARNING: Except for infant rattle, contents are not toyes. Keep out of reach of children.

Actual product styling and colors may vary. Please retain this packaging for future reference.

The First Years
c 2008 Learning Curve Brands, Inc.
100 Technology Center Drive
Stoughton, MA 02072, U.S.A.
All rights reserved
Made in India. ARC7058
Y705IC-OPL_BACK

Contents:
1 Emergency First Aid Guide
60 Adhesive Bandages
10 Triple Antibiotic Ointment packets
18 Sterile Gauze Pads (2x2, 3x3, 4x4)
2 Sterile Roller Bandages (3"w,4"w)
1 Adhesive Tape
1 Scissors
1 Tweezers
1 Mini-flashlight (2 AAA batteries included)
1 Instant Cold Pack
10 Alcohol Pads
10 Waterless Hand Sanitizers
1 Small, Cloth Blanket
1 Nasal Aspirator
1 Infant Toy Rattle
1 Travel/Storage Case

Product usage and care instructions inside
Refer to warning on individual products contained with this kit